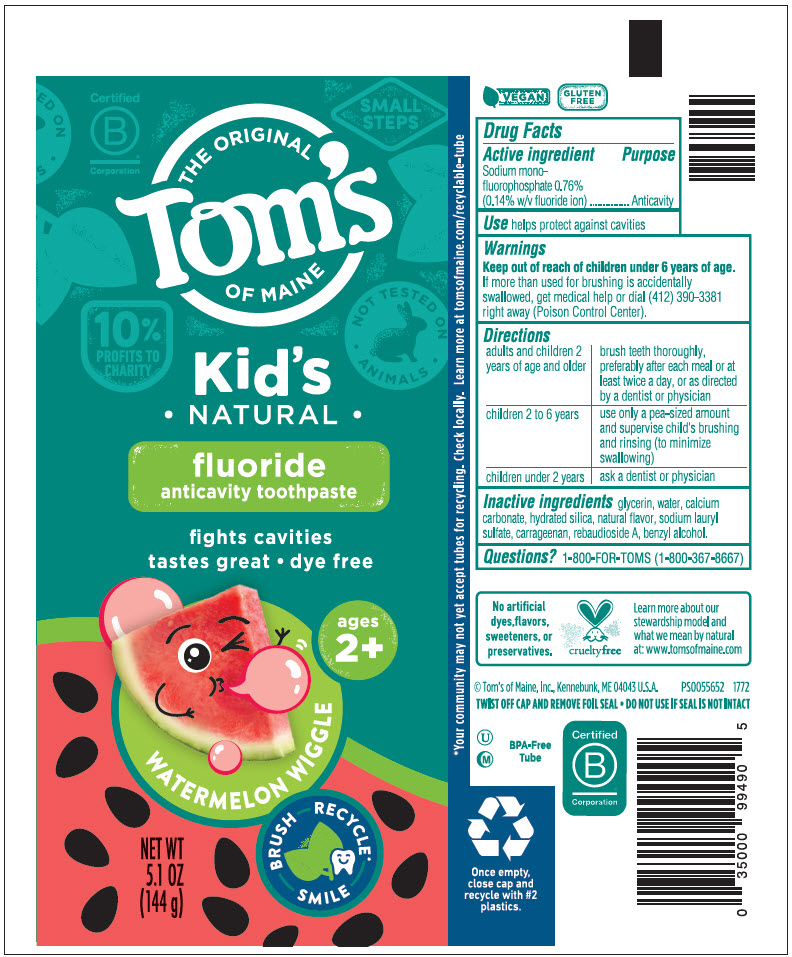 DRUG LABEL: Toms Kids Watermelon Wiggle
NDC: 51009-854 | Form: PASTE, DENTIFRICE
Manufacturer: Tom's of Maine, Inc.
Category: otc | Type: HUMAN OTC DRUG LABEL
Date: 20241024

ACTIVE INGREDIENTS: SODIUM MONOFLUOROPHOSPHATE 1.1 mg/1 g
INACTIVE INGREDIENTS: GLYCERIN; WATER; CALCIUM CARBONATE; HYDRATED SILICA; CARRAGEENAN; SODIUM LAURYL SULFATE; BENZYL ALCOHOL; REBAUDIOSIDE A

Tom's Kid's Watermelon Wiggle

Drug Facts

Active ingredient

Sodium monofluorophosphate 0.76% (0.14% w/v fluoride ion)

Purpose

Anticavity

Use

helps protect against cavities

Warnings

Keep out of reach of children under 6 years of age. If more than used for brushing is accidentally swallowed, get medical help or dial (412) 390-3381 right away (Poison Control Center).

Directions

adults and children 2 years of age and older | brush teeth thoroughly, preferably after each meal or at least twice a day, or as directed by a dentist or physician
children 2 to 6 years | use only a pea-sized amount and supervise child's brushing and rinsing (to minimize swallowing)
children under 2 years | ask a dentist or physician

Inactive ingredients

glycerin, water, calcium carbonate, hydrated silica, natural flavor, sodium lauryl sulfate, carrageenan, rebaudioside A, benzyl alcohol.

Questions?

1-800-FOR-TOMS (1-800-367-8667)

PRINCIPAL DISPLAY PANEL - 144 g Tube Label

THE ORIGINAL
Tom's
OF MAINE

Kid's
• NATURAL •

fluoride
anticavity toothpaste

fights cavities
tastes great • dye free

ages
2+

WATERMELON WIGGLE

NET WT
5.1 OZ
(144 g)

BRUSH
RECYCLE*
SMILE